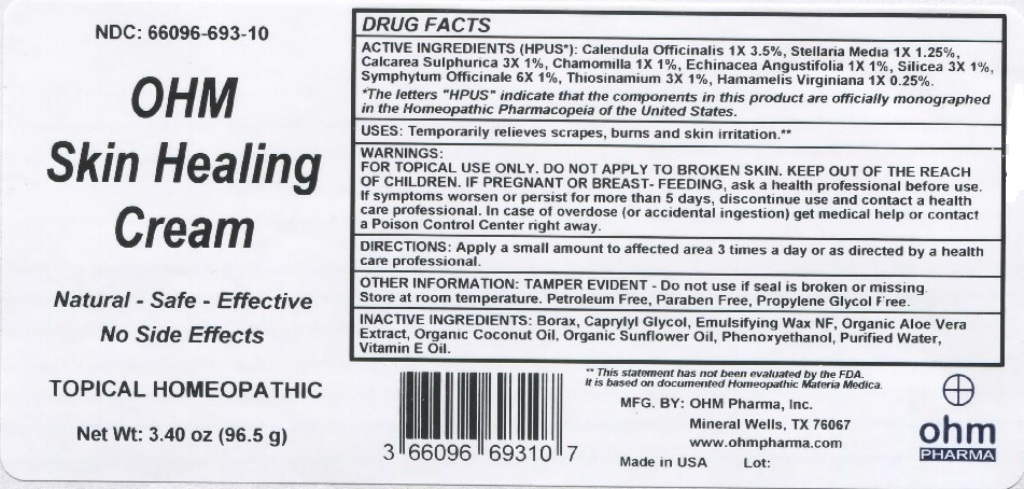 DRUG LABEL: OHM Skin Healing Cream
NDC: 66096-693 | Form: CREAM
Manufacturer: OHM PHARMA INC.
Category: homeopathic | Type: HUMAN OTC DRUG LABEL
Date: 20211229

ACTIVE INGREDIENTS: CALENDULA OFFICINALIS FLOWERING TOP 1 [hp_X]/96.5 g; STELLARIA MEDIA 1 [hp_X]/96.5 g; CALCIUM SULFATE ANHYDROUS 3 [hp_X]/96.5 g; MATRICARIA RECUTITA 1 [hp_X]/96.5 g; ECHINACEA ANGUSTIFOLIA 1 [hp_X]/96.5 g; SILICON DIOXIDE 3 [hp_X]/96.5 g; COMFREY ROOT 6 [hp_X]/96.5 g; ALLYLTHIOUREA 3 [hp_X]/96.5 g; HAMAMELIS VIRGINIANA ROOT BARK/STEM BARK 1 [hp_X]/96.5 g
INACTIVE INGREDIENTS: SODIUM BORATE; CAPRYLYL GLYCOL; POLYSORBATE 60; ALOE VERA LEAF; COCONUT OIL; SUNFLOWER OIL; PHENOXYETHANOL; WATER; .ALPHA.-TOCOPHEROL

OHM Skin Healing Cream

ACTIVE INGREDIENT

ACTIVE INGREDIENTS (HPUS*): Calendula Officinalis 1X 3.5%, Stellaria Media 1X 1.25%, Calcarea Sulphurica 3X 1%, Chamomilla 1X 1%, Echinacea Angustifolia 1X 1%, Silicea 3X 1%, Symphytum Officinale 6X 1%, Thiosinamium 3X 1%, Hamamelis Virginiana 1X 0.25%.

*The letters "HPUS" indicate that the components in this product are officially monographed in the Homeopathic Pharmacopeia of the United States.

INDICATIONS AND USAGE

USUS: Temporarily relieves scrapes, burns and skin irritation.**

**This statement has not been evaluated by the FDA. It is based on documented Homeopathic Materia Medica.

WARNINGS

WARNINGS: FOR TOPICAL USE ONLY. DO NOT APPLY TO BROKEN SKIN. IF PREGNANT OR BREAST-FEEDING, ask a health professional before use. If symptoms worsen or persist for more than 5 days, discontinue use and contact a health care professional. In case of overdose (or accidental ingestion) get medical help or contact a Poison Control Center right away.

- KEEP OUT OF THE REACH OF CHILDREN.

DOSAGE AND ADMINISTRATION

DIRECTIONS: Apply a small amount to affected area 3 times a day or as directed by a health care professional.

OTHER INFORMATION: TAMPER EVIDENT - Do not use if seal is broken or missing. Store at room temperature. Petroleum Free, Paraben Free, Propylene Glycol Free.

INACTIVE INGREDIENT

INAVTIVE INGREDIENTS: Borax, Caprylyl Glycol, Emulsifying Wax NF, Organic Aloe Vera Extract, Organic Coconut Oil, Organic Sunflower Oil, Phenoxyethanol, Purified Water, Vitamin E Oil.

QUESTIONS

MFG. BY: OHM Pharma, Inc. Mineral Wells, TX 76067. www.ohmpharma.com

PACKAGE LABEL

NDC: 66096-693-10

OHM Skin Healing Cream

Natural - Safe - Effective

No Side Effects

TOPICAL HOMEOPATHIC

Net Wt: 3.40oz (96.5g)

Made In USA

PURPOSE

Relieves Scrapes, burns and skin irritation.